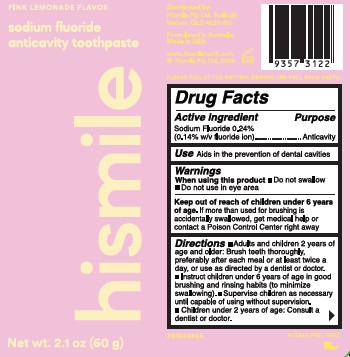 DRUG LABEL: HISMILE
NDC: 44038-0324 | Form: GEL
Manufacturer: Accupac LLC
Category: otc | Type: HUMAN OTC DRUG LABEL
Date: 20241204

ACTIVE INGREDIENTS: SODIUM FLUORIDE 0.243 g/100 g
INACTIVE INGREDIENTS: POTASSIUM PYROPHOSPHATE; XANTHAN GUM; GLYCERIN; LAURYL GLUCOSIDE; METHYL DIISOPROPYL PROPIONAMIDE; SODIUM LAUROYL SARCOSINATE; XYLITOL; D&C RED NO. 33; CARBOXYMETHYLCELLULOSE SODIUM, UNSPECIFIED FORM; SUCRALOSE; ZINC LACTATE; HYDRATED SILICA; SODIUM GLUCONATE; WATER; SORBITOL; 1,2-HEXANEDIOL; SODIUM PHOSPHATE

Active ingredient

Sodium fluoride 0.243%

(0.14 w/v fluoride ion)

Purpose

Anticavity

Use

Aids in the prevention of dental cavities

Warnings

When using this product

Do not swallow

Do not use in eye area

Keep out of the reach of children under 6 years of age

If more than used for brushing is swallowed, get medical help or contact a Poison Control Center right away.

Directions

Adults and children 2 years of age and older: Brush teeth thoroughly, preferably after each meal or at least twice a day, or use as directed by a dentist or doctor.

Instruct children under 6 years of age in good brushing and rinsing habtis (to minimize swallowing).

Supervise children as necessary until capable of using without supervision.

Children under 2 years of age: Consult a dentist or doctor.

Inactive ingredients

Water

Sorbitol

Glycerin

Hydrated Silica

Xylitol

Sodium Phosphate

Xanthan Gum

Sodium Lauroyl Sarcosinate

Tetrapotassium Pyrophosphate

1,2-Hexanediol

Cellulose Gum

Sucralose

Lauryl Glucoside

Methyl Diisopropyl Propionamide

Sodium Gluconate

Zinc Lactate

D&C Red No. 33